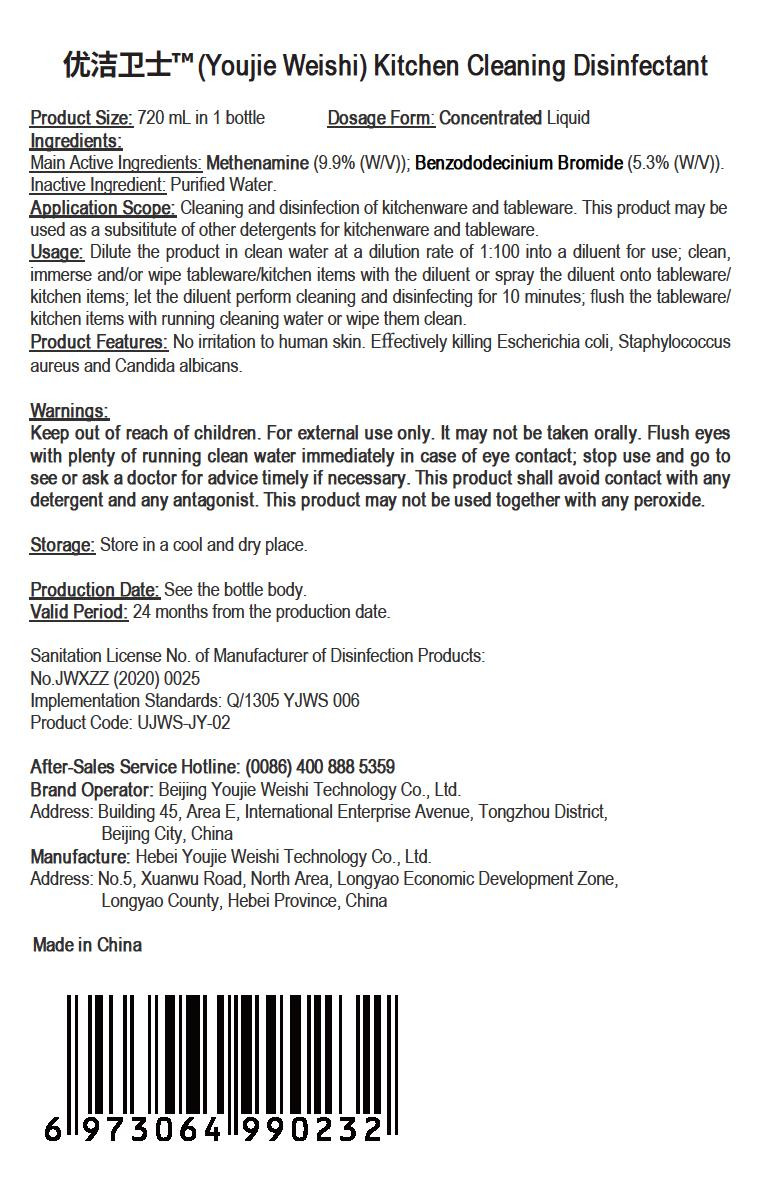 DRUG LABEL: Youjie Weishi Kitchen Cleaning Disinfectant
NDC: 55455-007 | Form: LIQUID
Manufacturer: Hebei Youjie Weishi Technology Co., Ltd.
Category: otc | Type: HUMAN OTC DRUG LABEL
Date: 20200507

ACTIVE INGREDIENTS: BENZODODECINIUM BROMIDE 38.16 g/720 mL; METHENAMINE 71.28 g/720 mL
INACTIVE INGREDIENTS: WATER

PURPOSE

Disinfection
Sterilization
No Rinseing

INACTIVE INGREDIENT

water

DOSAGE AND ADMINISTRATION

This product shall be stored in a cool, dry place.

ACTIVE INGREDIENT

Hexamethylenetetramine

Benzalkonium Bromide

keep out of reach of children

INDICATIONS AND USAGE

Dilute the product in clean water at a dilution rate of 1:100 into a diluent for use, clean,immerse and/or wipe tableware/kitchen items with the diluent or spray the diluent onto tableware/kitchen items; let the diluent perform cleaning and disinfecting for 10 minutes, flush the tableware/kitchen items with running cleaning water or wipe them clean.

WARNINGS

This product is a disinfectant for external use, and may not be taken orally; it must be kept out of reach of children. This product shall avoid contact with any detergent and antagonist drug. This product cannot be used together with peroxide.